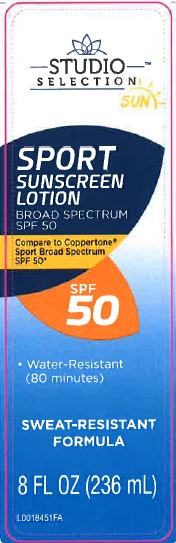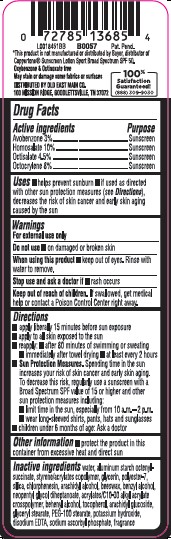 DRUG LABEL: Sunscreen
NDC: 55910-924 | Form: LOTION
Manufacturer: Old East Main Co.
Category: otc | Type: HUMAN OTC DRUG LABEL
Date: 20260302

ACTIVE INGREDIENTS: AVOBENZONE 30 mg/1 mL; HOMOSALATE 100 mg/1 mL; OCTISALATE 45 mg/1 mL; OCTOCRYLENE 80 mg/1 mL
INACTIVE INGREDIENTS: WATER; ALUMINUM STARCH OCTENYLSUCCINATE; STYRENE/ACRYLAMIDE COPOLYMER (500000 MW); GLYCERIN; POLYESTER-7; SILICON DIOXIDE; CHLORPHENESIN; ARACHIDYL ALCOHOL; YELLOW WAX; BENZYL ALCOHOL; NEOPENTYL GLYCOL DIHEPTANOATE; CARBOMER INTERPOLYMER TYPE A (ALLYL SUCROSE CROSSLINKED); DOCOSANOL; TOCOPHEROL; ARACHIDYL GLUCOSIDE; GLYCERYL MONOSTEARATE; PEG-100 STEARATE; POTASSIUM HYDROXIDE; EDETATE DISODIUM ANHYDROUS; SODIUM ASCORBYL PHOSPHATE

Studio Selection 924.000/924AA
Sport Sunscreen Lotion SPF 50

active ingredients

Avobenzone 3%

Homosalate 10%

Octisalate 4.5%

Octocrylene 8%

Purpose

Sunscreen

Uses

- helps prevent sunburn
- if used as directed with other sun protection measures (See Directions), decreases the risk of skin cancer and early skin aging caused by the sun

Warnings

For external use only

Do not use

- on damaged or broken skin

When using this product

- keep out of eyes. Rinse with water to remove.

Stop use and ask a doctor if

- rash occurs

Keep out of reach of children.

If swallowed, get medical help or contact a Poison Control right away.

Directions

- apply liberaly 15 minutes before sun exposure
- apply to all skin exposed to the sun
- reapply:
- after 80 minutes of swimming or sweating
- immediately after towel drying
- at least every 2 hours
- Sun Protection Measures. Spending time in the sun increases your risk of skin cancer and early skin aging. To decrease this risk, regularly use a sunscreen with Broad Spectrum SPF value of 15 or higher and other sun protection measures including:
- limit time in the sun, especialy from 10 a.m. -2 p.m.
- wear long-sleeved shirts, pants, hats and sunglasses
- children under 6 months of age: Ask a doctor

Other information

- protect the product in this container from excessive heat and direct sun

inactive ingredients

water, aluminum starch octenylsuccinate, styrene/acrylates copolymer, glycerin, polyester-7, silica, chlorphenesin, arachidyl alcohol, beeswax, benzyl alcohol, neopentyl glycol diheptanoate, acrylates/C10-30 alkyl acrylate crosspolymer, behenyl alcohol, tocopherol, arachidyl glucoside, glyceryl stearate, PEG-100 stearate, potassium hydroxide, disodium EDTA, sodium ascorbyl phosphate, fragrance

claims

*This product is not manufactured or distributed by Bayer, distributor of Coppertone®Sunscreen Lotion Spectrum SPF 50.

Oxybenzone & Octinoxate Free

May stain or damage some fabrics or surfaces

ADVERSE REACTION

DISTRIBUTED BY OLD EAST MAIN CO.

100 MISSION RIDGE, GOODLETTSVILLE, TN 37072

100% Satisfaction Guaranteed!

(888) 309-9030

principal display panel

STUDIO SELECTION™

SUN

SPORT

SUNSCREEN

LOTION

BROAD SPECTRUM

SPF 50

Compare to Coppertone®Sport Broad Spectrum SPF 50*

SPF 50

- Water-Resistant (80 minutes)

SWEAT-RESISTANT

FORMULA

8 FL OZ (236 mL)